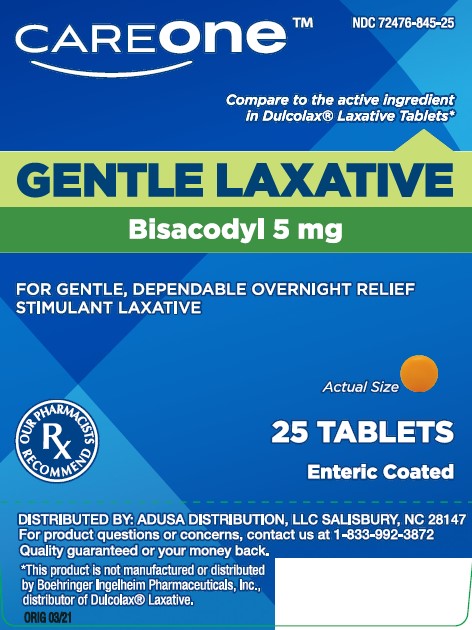 DRUG LABEL: STIMULANT LAXATIVE
NDC: 72476-845 | Form: TABLET, DELAYED RELEASE
Manufacturer: RETAIL BUSINESS SERVICES, LLC
Category: otc | Type: HUMAN OTC DRUG LABEL
Date: 20241220

ACTIVE INGREDIENTS: BISACODYL 5 mg/1 1
INACTIVE INGREDIENTS: CALCIUM SULFATE ANHYDROUS; ANHYDROUS LACTOSE; CARNAUBA WAX; SILICON DIOXIDE; STARCH, CORN; D&C YELLOW NO. 10; FD&C YELLOW NO. 6; GELATIN; FERROSOFERRIC OXIDE; ACACIA; FERRIC OXIDE YELLOW; MAGNESIUM STEARATE; CELLULOSE, MICROCRYSTALLINE; POLYETHYLENE GLYCOL 400; POLYVINYL ACETATE PHTHALATE; POVIDONE; SHELLAC; SODIUM STARCH GLYCOLATE TYPE A CORN; STEARIC ACID; SUCROSE; TALC; TITANIUM DIOXIDE

CARE ONE GENTLE LAXATIVE

Active ingredient

(In each tablet)

Bisacodyl 5mg

Purpose

Stimulant Laxative

Uses

- relieves occasional constipation and irregularity
- this product generally produces a bowel movement in 6 to 12 hours

Warnings

Do not use if you cannot swallow without chewing
Ask a doctor before use if you have
■ stomach pain, nausea or vomiting
■ a sudden change in bowel habits that lasts more than 2 weeks
When using this product
■ do not chew or crush tablet(s)
■ it may cause stomach discomfort, faintness and
cramps
■ do not use within 1 hour after taking an antacid
or milk

Stop use and ask a doctor if

■ you have rectal bleeding or no bowel movement
after using this product. These could be signs of
a serious condition.
■ you need to use a laxative for more than 1 week

If pregnant or breast-feeding,

ask a health professional before use.

Keep out of reach of children.

In case of overdose, get medical help or contact a Poison Control Center right away 1(800) 222-1222.

DOSAGE AND ADMINISTRATION

- take with a glass of water
- adults and children 12 years and over: take 1 to 3 tablets in a single daily dose
- children 6 to under 12 years: take 1 tablet in a single daily dose
- children under 6 years: ask a doctor

Inactive ingredients

Acadia, Anhydrous Calcium Sulfate, Anhydrous Lactose, Carnauba Wax, Colloidal Silicon Dioxide, Corn Starch, D&C Yellow #10 Aluminum Lake, FD&C yellow #6 aluminum lake, Gelatin, Iron Oxide, Iron Oxide Black, Iron Oxide Yellow(Iron Oxide Ochre), Magnesium Stearate, Microcrystalline Cellulose, Polyethylene Glycol (PEG) 400, Polyvinyl Acetate Phthalates, Povidone, Shellac, Sodium Starch Glycolate, Stearic Acid, Sugar, Talc, Titanium Dioxide

Questions or comments?

1-888-333-9792

DISPLAY PANEL

GENTLE LAXATIVE

BISACODYL 5 mg

GENTLE YET EFFECTIVE STIMULANT LAXATIVE

25 TABLETS

ENTERIC COATED